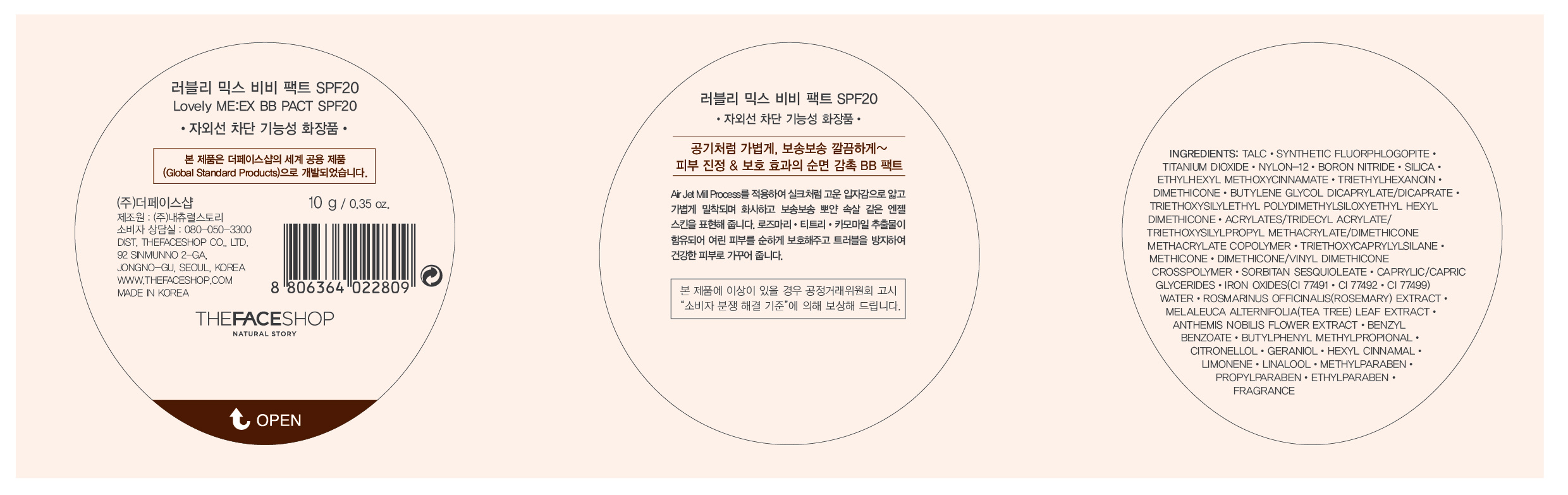 DRUG LABEL: Lovely ME EX BB PACT SPF20
NDC: 51523-114 | Form: POWDER
Manufacturer: THEFACESHOP CO., LTD
Category: otc | Type: HUMAN OTC DRUG LABEL
Date: 20110901

ACTIVE INGREDIENTS: TITANIUM DIOXIDE 13.852 g/100 g; OCTINOXATE 2 g/100 g
INACTIVE INGREDIENTS: TALC; DIMETHICONE; TRIETHOXYCAPRYLYLSILANE; BORON NITRIDE; SILICON DIOXIDE; TRIETHYLHEXANOIN; FERRIC OXIDE RED; SORBITAN SESQUIOLEATE; FERRIC OXIDE YELLOW; FERROSOFERRIC OXIDE; WATER; BUTYLENE GLYCOL; MELALEUCA ALTERNIFOLIA LEAF; CHAMAEMELUM NOBILE FLOWER; METHYLPARABEN; PROPYLPARABEN; ETHYLPARABEN

Lovely ME:EX BB PACT SPF20

ACTIVE INGREDIENT

TITANIUM DIOXIDE (13.852%)
OCTINOXATE (2%)

WARNINGS AND PRECAUTIONS

For external use only

Keep out of reach of children. Is swallowed, get medical help or contact a Poison Control Center right away.

WHEN USING

Keep out of eyes. Rinse with water to remove.

Stop use if a rash or irritation develops and lasts.

PACKAGE LABEL

Lovely ME:EX BB PACT SPF20